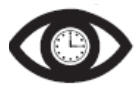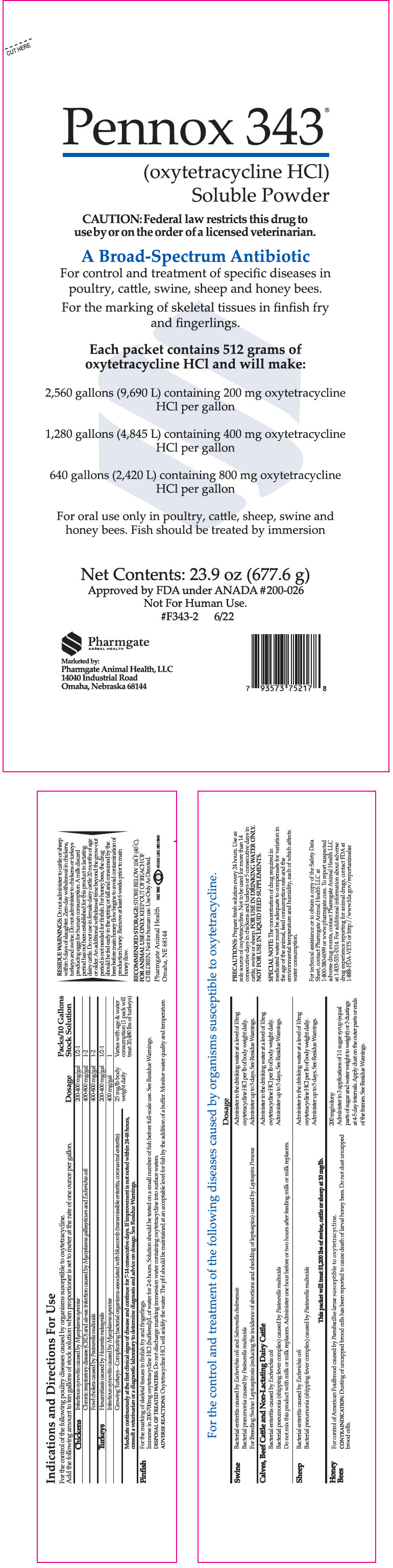 DRUG LABEL: Pennox 343
NDC: 51429-343 | Form: POWDER
Manufacturer: Pharmgate Animal Health
Category: animal | Type: PRESCRIPTION ANIMAL DRUG LABEL
Date: 20221018

ACTIVE INGREDIENTS: Oxytetracycline Hydrochloride 0.756 g/1000 g

Pennox 343®
(oxytetracycline HCl)
Soluble Powder

PRECAUTIONS

PRECAUTIONS: Prepare fresh solution every 24 hours. Use as sole source of oxytetracycline. Not to be used for more than 14 consecutive days in chickens and turkeys or 5 consecutive days in cattle, swine or sheep. FOR USE IN DRINKING WATER ONLY. NOT FOR USE IN LIQUID FEED SUPPLEMENTS.

SPECIAL NOTE: The concentration of drug required in medicated water must be adequate to compensate for variation in the age of the animal, feed consumption rate and the environmental temperature and humidity, each of which aﬀects water consumption.

RESIDUE WARNING

RESIDUE WARNINGS: Do not administer to cattle or sheep within 5 days of slaughter. Zero day withdrawal in chickens, turkeys and swine. Do not administer to chickens or turkeys producing eggs for human consumption. A milk discard period has not been established for this product in lactating dairy cattle. Do not use in female dairy cattle 20 months of age or older. An additional withdrawal time beyond the grow-out period is not needed for ﬁnﬁsh. For honey bees, the drug should be fed early in the spring or fall and consumed by the bees before main honey ﬂow begins to avoid contamination of production honey. Remove at least 6 weeks prior to main honey ﬂow.

RECOMMENDED STORAGE: STORE BELOW 104°F (40°C).
FOR ANIMAL USE ONLY. KEEP OUT OF REACH OF CHILDREN.

Not for human use. Use Only As Directed.

For the control and treatment of the following diseases caused by organisms susceptible to oxytetracycline.

Indications and Directions For Use

For the control of the following poultry diseases caused by organisms susceptible to oxytetracycline.

Add the following amount to ten gallons of stock solution when proportioner is set to meter at the rate of one ounce per gallon.

Chickens | Dosage | Packs/10 Gallons Stock Solution
Infectious synovitis caused by Mycoplasma synoviae | 200-400 mg/gal | ½ - 1
Chronic respiratory disease (CRD) and air-sac infection caused by Mycoplasma gallisepticum and Escherichia coli | 400-800 mg/gal | 1-2
Fowl cholera caused by Pasteurella multocida | 400-800 mg/gal | 1-2
Turkeys
Hexamitiasis caused by Hexamita meleagridis | 200-400 mg/gal | ½ - 1
Infectious synovitis caused by Mycoplasma synoviae | 400 mg/gal | 1
Growing Turkeys – Complicating bacterial organisms associated with bluecomb (transmissible enteritis, coronaviral enteritis) | 25 mg/lb body weight daily | Varies with age & water consumption (1 pack will treat 20,480 lbs of turkeys)
Medicate continuously at the ﬁrst clinical signs of disease and continue for 7-14 consecutive days. If improvement is not noted within 24-48 hours, consult a veterinarian or a diagnostic laboratory to determine diagnosis and advice on dosage. See Residue Warnings.
Finfish
For the marking of skeletal tissues in ﬁnﬁsh fry and ﬁngerlings.
Immerse in 200-700mg oxytetracycline HCl (buffered)/L of water for 2-6 hours. Solution should be tested on a small number of ﬁsh before full-scale use. See Residue Warnings.
DISPOSAL OF TREATED WATERS: Do not discharge marking immersion water containing oxytetracycline into surface waters.
ADVERSE REACTIONS: Oxytetracycline HCl will acidify the water. The pH should be maintained at an acceptable level for ﬁsh by the addition of a buffer. Monitor water quality and temperature.

Swine | Dosage
Bacterial enteritis caused by Escherichia coli and Salmonella choleraesuis Bacterial pneumonia caused by Pasteurella multocida For Breeding Swine: Leptospirosis (reducing the incidence of abortions and shedding of leptospira) caused by Leptospira Pomona | Administer in the drinking water at a level of 10 mg oxytetracycline HCl per lb of body weight daily. Administer up to 5 days. See Residue Warnings.
Calves, Beef Cattle and Non-Lactating Dairy Cattle
Bacterial enteritis caused by Escherichia coli Bacterial pneumonia (shipping fever complex) caused by Pasteurella multocida Do not mix this product with milk or milk replacers. Administer one hour before or two hours after feeding milk or milk replacers. | Administer in the drinking water at a level of 10mg oxytetracycline HCl per lb of body weight daily. Administer up to 5 days. See Residue Warnings.
Sheep
Bacterial enteritis caused by Escherichia coli Bacterial pneumonia (shipping fever complex) caused by Pasteurella multocida | Administer in the drinking water at a level of 10mg oxytetracycline HCl per lb of body weight daily. Administer up to 5 days. See Residue Warnings.
This packet will treat 51,200 lbs of swine, cattle or sheep at 10 mg/lb.

Honey Bees

For control of American Foulbrood caused by Paenibacillus larvae susceptible to oxytetracycline.
CONTRAINDICATION: Dusting of uncapped brood cells has been reported to cause death of larval honey bees. Do not dust uncapped brood cells.

200 mg/colony
Administer in 3 applications of 1:1 sugar syrup (equal parts of sugar and water weight to weight) or 3 dustings at 4-5 day intervals. Apply dust on the outer parts or ends of the frames. See Residue Warnings.

For technical assistance or to obtain a copy of the Safety Data Sheet, contact Pharmgate Animal Health LLC at 1-800-380-6099 or www.pharmgate.com. To report suspected adverse drug events, contact Pharmgate Animal Health LLC at 1-833-531-0114. For additional information about adverse drug experience reporting for animal drugs, contact FDA at 1-888-FDA-VETS or http://www.fda.gov/reportanimalae

Take TimeObserve Directions

PRINCIPAL DISPLAY PANEL - 677.6 g Pouch Label

CUT HERE

Pennox 343®
(oxytetracycline HCl)
Soluble Powder

CAUTION: Federal law restricts this drug to
use by or on the order of a licensed veterinarian.

A Broad-Spectrum Antibiotic

For control and treatment of specific diseases in
poultry, cattle, swine, sheep and honey bees.
For the marking of skeletal tissues in finfish fry
and fingerlings.

Each packet contains 512 grams of
oxytetracycline HCl and will make:

2,560 gallons (9,690 L) containing 200 mg oxytetracycline
HCl per gallon

1,280 gallons (4,845 L) containing 400 mg oxytetracycline
HCl per gallon

640 gallons (2,420 L) containing 800 mg oxytetracycline
HCl per gallon

For oral use only in poultry, cattle, sheep, swine and
honey bees. Fish should be treated by immersion

Net Contents: 23.9 oz (677.6 g)
Approved by FDA under ANADA # 200-026
Not For Human Use.
#F343-2
6/22

Pharmgate
ANIMAL HEALTH

Marketed by:
Pharmgate Animal Health, LLC
14040 Industrial Road
Omaha, Nebraska 68144